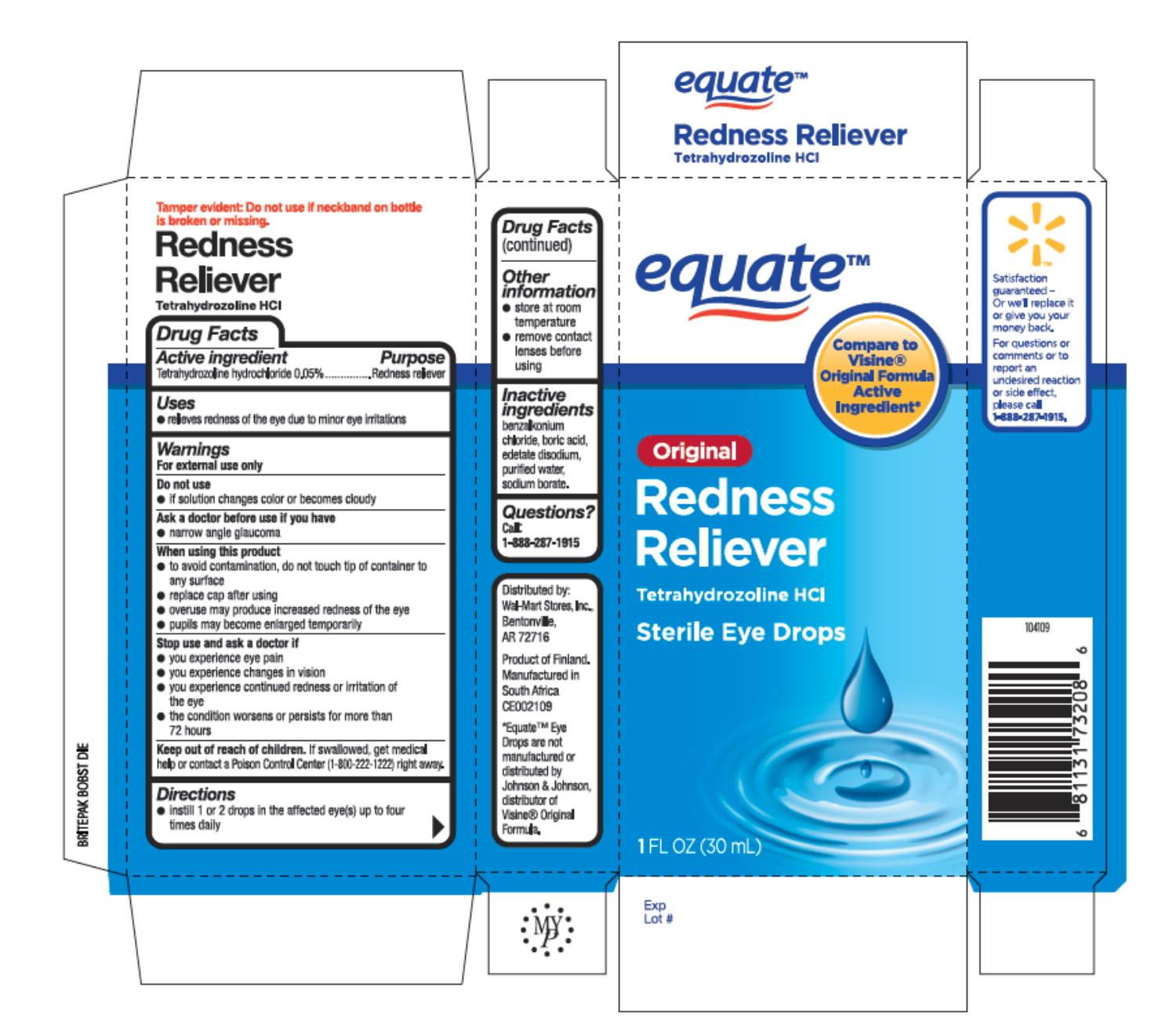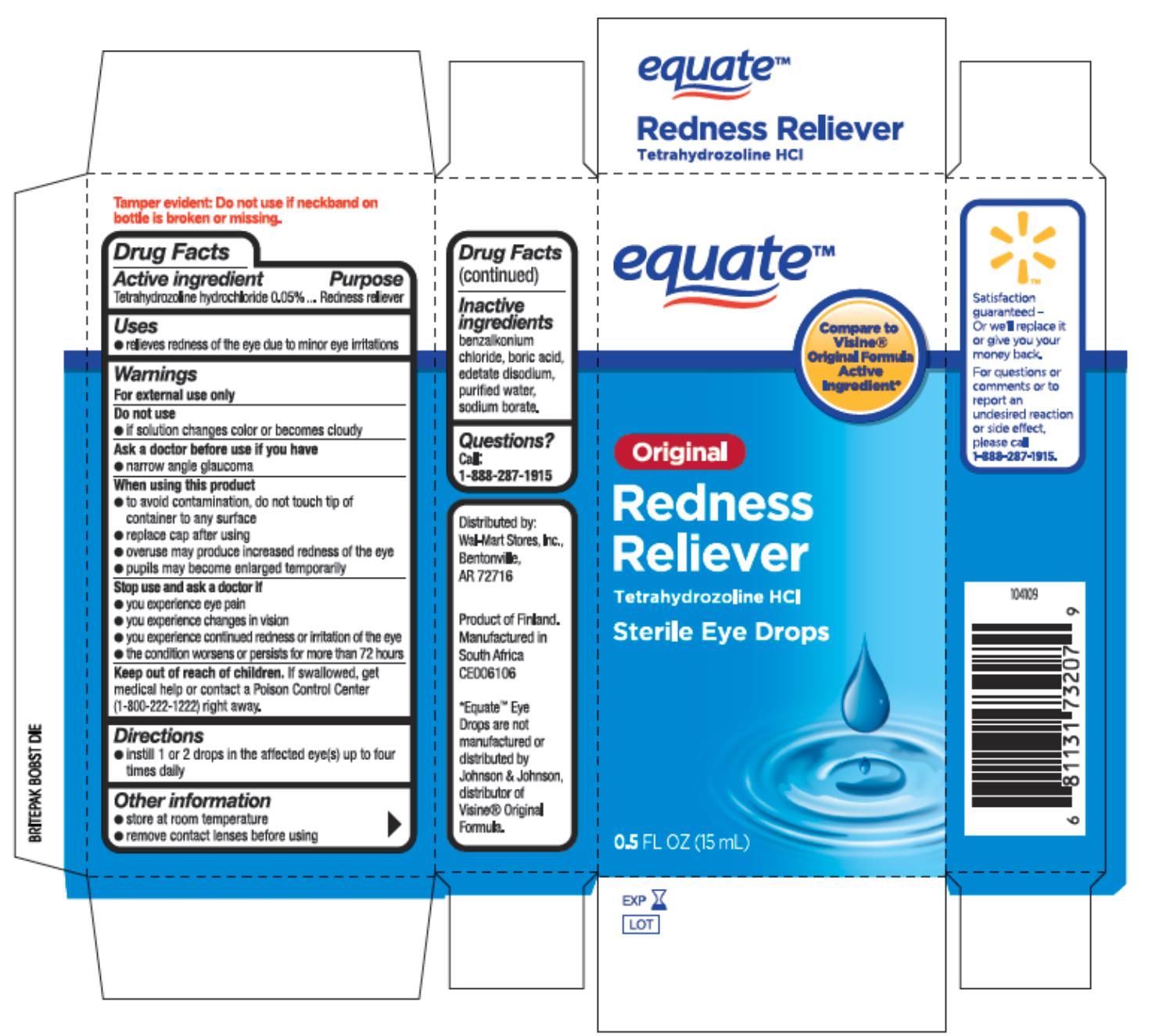 DRUG LABEL: Equate Eye Drops
NDC: 67172-282 | Form: LIQUID
Manufacturer: Prestige Brands Holdings, Inc.
Category: otc | Type: HUMAN OTC DRUG LABEL
Date: 20241025

ACTIVE INGREDIENTS: TETRAHYDROZOLINE HYDROCHLORIDE 0.5 mg/1 mL
INACTIVE INGREDIENTS: BENZALKONIUM CHLORIDE; BORIC ACID; EDETATE DISODIUM; WATER; SODIUM BORATE

Equate Eye Drops

Drug Facts

Active ingredient

Tetrahydrozoline Hydrochloride 0.05%

Purpose

Redness reliever

Uses

- relieves redness of the eye due to minor eye irritations

Warnings

For external use only

Do not use

- if solution changes color or becomes cloudy

Ask a doctor before use if you have

- narrow angle glaucoma

When using this product

- to avoid contamination, do not touch tip of container to any surface
- replace cap after using
- overuse may produce increased redness of the eye
- pupils may become enlarged temporarily

Stop use and ask a doctor if

- you experience eye pain
- you experience changes in vision
- you experience continued redness or irritation of the eye
- the condition worsens or persists for more than 72 hours

Keep out of reach of children.

If swallowed, get medical help or contact a Poison Control Center (1-800-222-1222) right away.

Directions

- instill 1 to 2 drops in the affected eye(s) up to four times daily

Other information

- store at room temperature
- remove contact lenses before using

Inactive ingredients

benzalkonium chloride, boric acid, edetate disodium, purified water, sodium borate

Questions?

1-888-287-1915

Principal Display Panel

Equate®
Original Redness Reliever
Tetrahydrozoline HCI
Sterile Eye Drops
1 FL OZ (30 mL)

Principal Display Panel

Equate®
Original Redness
Reliever
Tetrahydrozoline HCI
Sterile Eye Drops
0.5 FL OZ (15 mL)